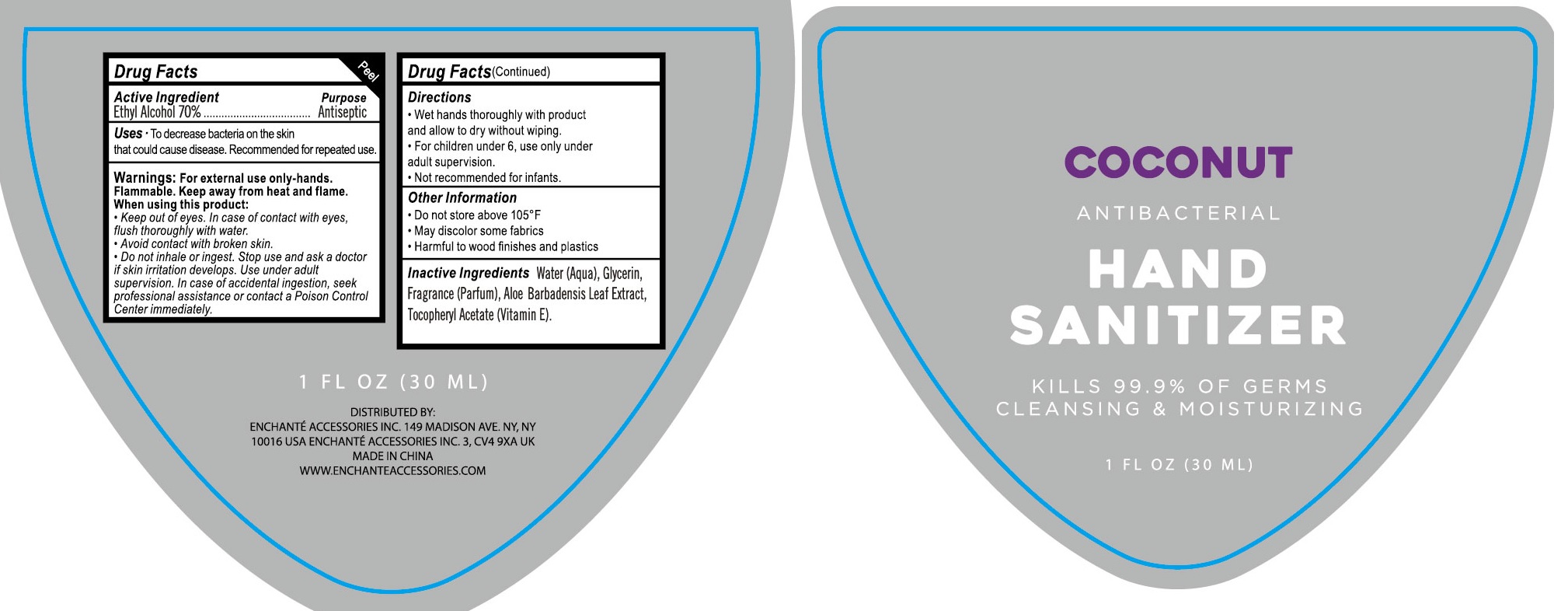 DRUG LABEL: COCONUT HAND SANITIZER

NDC: 56136-532 | Form: SPRAY
Manufacturer: Ganzhou Olivee Cosmetic Co., Ltd.
Category: otc | Type: HUMAN OTC DRUG LABEL
Date: 20251125

ACTIVE INGREDIENTS: ALCOHOL 70 mL/100 mL
INACTIVE INGREDIENTS: WATER; GLYCERIN; .ALPHA.-TOCOPHEROL ACETATE, DL-; ALOE VERA LEAF

SPRAY HAND SANITIZER

Active ingredient

Ethyl Alcohol ...... 70%

Purpose

Antiseptic

Use

To decrease bacteria on the skin that could cause disease.

Recommended for repeated use.

Warnings

For external use only-hands.

Flammable.Keep away from heat and flame.

When using this product

- Keep out of eyes. In case of contact with eyes, flush thoroughly with water.
- Avoid contact with broken skin.
- Do not inhale or ingest. Stop use and ask a doctor if skin irritation develops. Use under adult supervision. In case of accidental ingestion, seek professional assistance or contact a Poison Control Center Immediately.

Keep out of reach of children.

Contact a Poison Control Center immediately.

Directions

- Wet hands toroughly with product and allow to dry without wiping.
- Not recommended for infants.

Inactive ingredients

Water (Aqua), Glycerin, Fragrance (Parfum), Aloe Barbadensis Leaf Extract, Tocopheryl Actate (Vitamin E).

Other information:

- Do not Store above 105℉.
- May discolor some fabrics.
- Harmful to wood finisheds and plastics